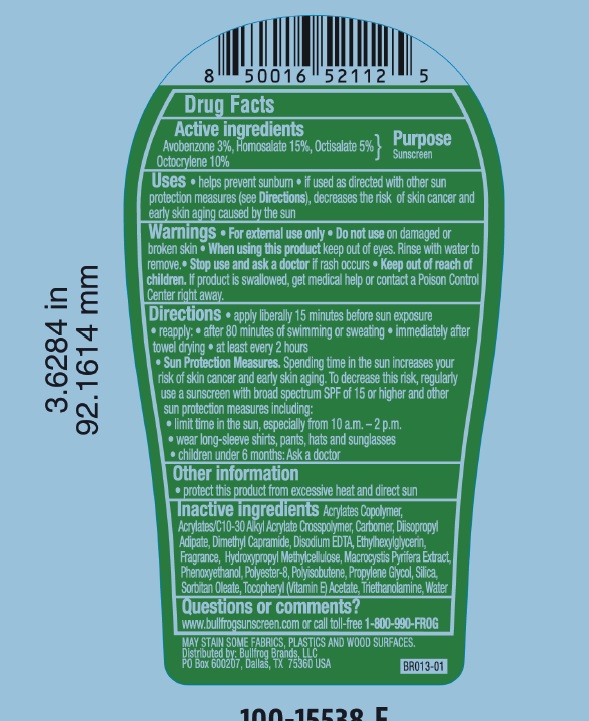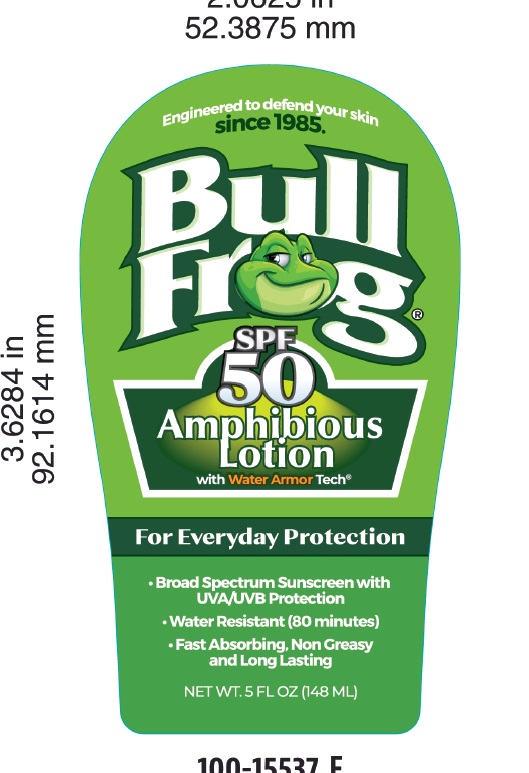 DRUG LABEL: Sunscreen and Amphibious
NDC: 77714-004 | Form: LOTION
Manufacturer: Bullfrog Brands, LLC
Category: otc | Type: HUMAN OTC DRUG LABEL
Date: 20240125

ACTIVE INGREDIENTS: OCTISALATE 50 mg/1 g; HOMOSALATE 150 mg/1 g; OCTOCRYLENE 100 mg/1 g; AVOBENZONE 30 mg/1 g
INACTIVE INGREDIENTS: EDETATE DISODIUM ANHYDROUS; ETHYLHEXYLGLYCERIN; HYPROMELLOSES; POLYISOBUTYLENE (1300 MW); TROLAMINE; CARBOMER COPOLYMER TYPE B (ALLYL PENTAERYTHRITOL CROSSLINKED); BUTYL ACRYLATE/METHYL METHACRYLATE/METHACRYLIC ACID COPOLYMER (18000 MW); .ALPHA.-TOCOPHEROL ACETATE; DIISOPROPYL ADIPATE; DIMETHYL CAPRAMIDE; MACROCYSTIS PYRIFERA; PHENOXYETHANOL; PROPYLENE GLYCOL; SILICON DIOXIDE; SORBITAN MONOOLEATE; WATER

Bull Frog SPF50 Amphibious lotion with Armor Tech

Active ingredients

Avobenzone 3.0%, Octocrylene 10%, Homosalate 15%, Octisalate 5%

Purpose

Sunscreen

Uses

- helps prevent sunburn
- if used as directed with other sun protection measures, decreases the risk of skin cancer and early skin aging caused by the sun

Warnings

For external use only

Do not use on damaged or broken skin

when using this product keep out of eyes

Rinse with water to remove

Stop use and ask a doctor if rash occurs

keep out of reach of children

if product is swallowed, get medial help or contact a poison control center right away

FLAMMABLE:

• do not use near heat, flame or while smoking

• avoid long term storage above 104°F (40°C)

• do not puncture or incinerate

• contents under pressure

• do not store at temperatures above 120°F (49°C).

Do not use • on damaged or broken skin.

When using this product • keep out of eyes. Rinse with water to remove.

Stop use and ask a doctor if • rash occurs.

Keep out of reach of children. If swallowed, get medical help or contact a Poison Control Center right away.

Directions

- apply liberally 15 minutes before sun exposure
- reapply:

• after 80 minutes of swimming or sweating

• immediately after towel drying

• at least every 2 hours

- children under 6 months of age: ask a doctor

Other information

• Protect the product in this container from excessive heat and direct sun.

Inactive ingredients

Acrylates/Copolymer, Acrylates/C10-30 Alkyl acrylate crosspolymer, carbomer, diisoproyl adipate, dimethyl capramide, disodium EDTA,ethylhexylglycerin, fragrance, hydroxypropyl methylcellulose, macrocystis pyrifera extract, phenoxyethanol, polyster-8, polyisobutene, propylene glycol, silica, sorbitan oleate, Vitamin E, triethanolamine, water

Questions or Comments?

www.bullfrogsunscreen.com or call toll-free 1-800-990-FROG

PACKAGE LABEL

\